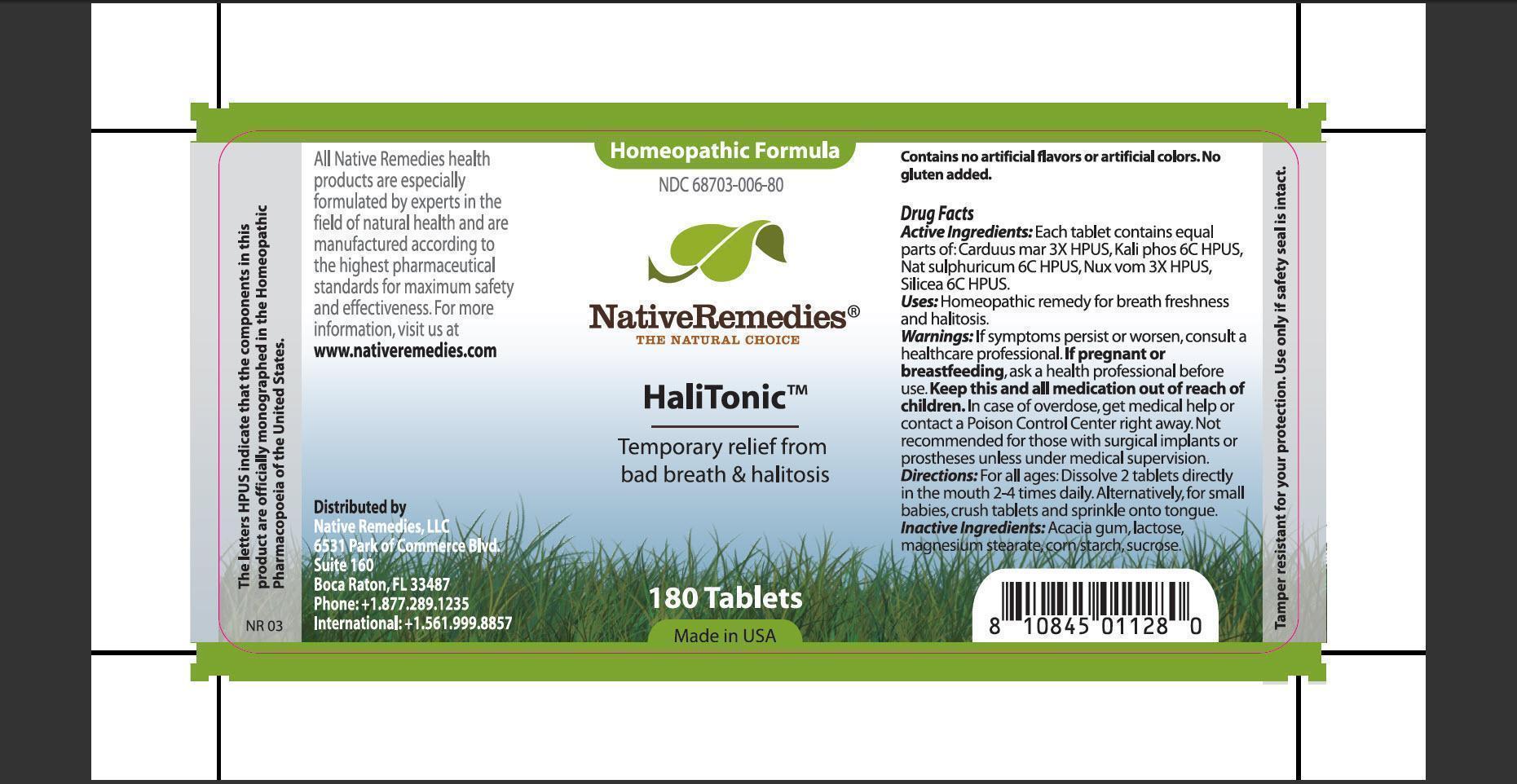 DRUG LABEL: HaliTonic
                
                
NDC: 68703-006 | Form: TABLET
Manufacturer: Native Remedies LLC
Category: homeopathic | Type: HUMAN OTC DRUG LABEL
Date: 20130102

ACTIVE INGREDIENTS: SILYBUM MARIANUM SEED 3 [hp_X]/1 1; POTASSIUM PHOSPHATE, DIBASIC 6 [hp_C]/1 1; SODIUM SULFATE 6 [hp_C]/1 1; STRYCHNOS NUX-VOMICA SEED 3 [hp_X]/1 1; SILICON DIOXIDE 6 [hp_C]/1 1
INACTIVE INGREDIENTS: ACACIA; LACTOSE; MAGNESIUM STEARATE; STARCH, CORN; SUCROSE

HaliTonic

PURPOSE

Temporary relief from bad breath and halitosis

ACTIVE INGREDIENT

Active Ingredients: Each tablet contains equal part of: Carduus mar 3X HPUS, Kali phos 6C HPUS, Nat sulphuricum 6C HPUS, Nux vom 3X HPUS, Silicea 6C HPUS.

INDICATIONS AND USAGE

Uses: Homeopathic remedy for breath freshness and halitosis.

WARNINGS

Warnings: If symptoms persist or worsen, consult a healthcare professional.

PREGNANCY OR BREAST FEEDING

If pregnant of breastfeeding, ask a health professional before use.

KEEP OUT OF REACH OF CHILDREN

Keep this and all medication out of reach of children.

OVERDOSAGE

In case of overdose, get medical help or contact a Poison Control Center right away. Not recommended for those with surgical implants or prostheses unless under medical supervision.

DOSAGE AND ADMINISTRATION

Directions: For all ages: Dissolve 2 tablets directly in the mouth 2-4 times daily. Alternatively, for small babies, crush tablets and sprinkle onto tongue.

INACTIVE INGREDIENT

Inactive Ingredients: Acacia gum, lactose,magnesium stearate, corn starch, sucrose.

PATIENT COUNSELING INFORMATION

The letters HPUS indicate that the components in this product are officially monographed in the Homeopathic Pharmacopoeia of the United States.

All Native Remedies health products are specially formulated by experts in the field of natural health and are manufactured according to the highest pharmaceutical standards for maximum safety and effectiveness. For more information, visit us at www.natiremedies.com

Distributed by
Native Remedies, LLC
6531 Park of Commerce Blvd.
Suite 160
Boca Raton, Fl 33487
Phone:+1.877.289.1235
International:+1.561.999.8857

Contains no artificial flavors or artificial color. No gluten added.

STORAGE AND HANDLING

Tamper resistant for your protection. Use only if safety seal is intact.